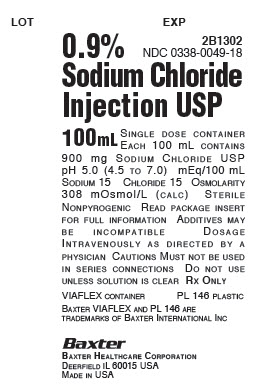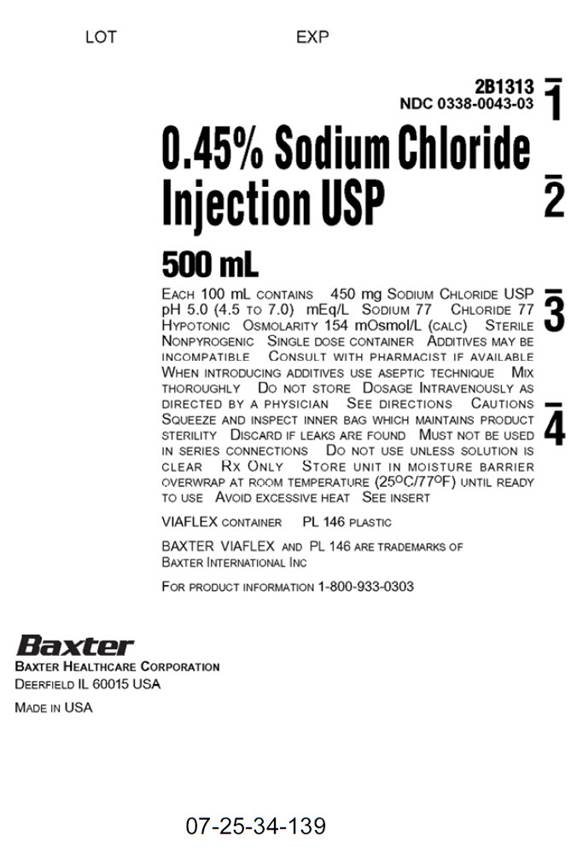 DRUG LABEL: Sodium Chloride
NDC: 0338-0049 | Form: INJECTION, SOLUTION
Manufacturer: Baxter Healthcare Corporation
Category: prescription | Type: HUMAN PRESCRIPTION DRUG LABEL
Date: 20240724

ACTIVE INGREDIENTS: SODIUM CHLORIDE 9 g/1000 mL
INACTIVE INGREDIENTS: WATER

Sodium Chloride Injection, USP
in VIAFLEX Plastic Container

DESCRIPTION

Sodium Chloride Injection, USP is a sterile, nonpyrogenic solution for fluid and electrolyte replenishment in single dose containers for intravenous administration. It contains no antimicrobial agents. The nominal pH is 5.0 (4.5 to 7.0). Composition, osmolarity, and ionic concentration are shown below:

0.45% Sodium Chloride Injection, USP contains 4.5 g/L Sodium Chloride, USP (NaCl) and is hypotonic with an osmolarity of 154 mOsmol/L (calc). It contains 77 mEq/L sodium and 77 mEq/L chloride.

0.9% Sodium Chloride Injection, USP contains 9 g/L Sodium Chloride, USP (NaCl) with an osmolarity of 308 mOsmol/L (calc). It contains 154 mEq/L sodium and 154 mEq/L chloride.

The VIAFLEX plastic container is fabricated from a specially formulated polyvinyl chloride (PL 146 Plastic). The amount of water that can permeate from inside the container into the overwrap is insufficient to affect the solution significantly. Solutions in contact with the plastic container can leach out certain of its chemical components in very small amounts within the expiration period, e.g., di-2- ethylhexyl phthalate (DEHP), up to 5 parts per million. However, the safety of the plastic has been confirmed in tests in animals according to USP biological tests for plastic containers as well as by tissue culture toxicity studies.

CLINICAL PHARMACOLOGY

Sodium Chloride Injection, USP has value as a source of water and electrolytes. It is capable of inducing diuresis depending on the clinical condition of the patient.

INDICATIONS AND USAGE

Sodium Chloride Injection, USP is indicated as a source of water and electrolytes.

0.9% Sodium Chloride Injection, USP is also indicated for use as a priming solution in hemodialysis procedures.

CONTRAINDICATIONS

None known.

WARNINGS

Hypersensitivity

Hypersensitivity and infusion reactions, including hypotension, pyrexia, tremor, chills, urticaria, rash, and pruritus have been reported with 0.9% Sodium Chloride Injection, USP and may occur with 0.45% Sodium Chloride Injection, USP.

Stop the infusion immediately if signs or symptoms of a hypersensitivity reaction develop, such as tachycardia, chest pain, dyspnea and flushing. Appropriate therapeutic countermeasures must be instituted as clinically indicated.

Electrolyte Imbalances

Fluid Overload

Depending on the volume and rate of infusion, and the patient’s underlying clinical condition, the intravenous administration of Sodium Chloride Injection, USP can cause fluid disturbances such as overhydration/hypervolemia and congested states, including pulmonary congestion and edema.

Avoid 0.9% Sodium Chloride Injection, USP in patients with or at risk for fluid and/or solute overloading. If use cannot be avoided, monitor fluid balance, electrolyte concentrations, and acid base balance, as needed and especially during prolonged use.

Hyponatremia

Sodium Chloride Injection, USP may cause hyponatremia. Hyponatremia can lead to acute hyponatremic encephalopathy characterized by headache, nausea, seizures, lethargy, and vomiting. Patients with brain edema are at particular risk of severe, irreversible and life-threatening brain injury.

The risk of hospital-acquired hyponatremia is increased in patients with cardiac or pulmonary failure, and in patients with non-osmotic vasopressin release (including SIADH) treated with high volume of Sodium Chloride Injection, USP.

The risk for hyponatremia is increased in pediatric patients, elderly patients, postoperative patients, those with psychogenic polydipsia, and in patients treated with medications that increase the risk of hyponatremia (such as diuretics, certain antiepileptic and psychotropic medications). See DRUG INTERACTIONS.

Patients at increased risk for developing complications of hyponatremia such as hyponatremic encephalopathy, include pediatric patients, women (in particular pre-menopausal women), patients with hypoxemia, and patients with underlying central nervous system disease. Avoid Sodium Chloride Injection, USP in patients with or at risk for hyponatremia. If use cannot be avoided, monitor serum sodium concentrations.

Rapid correction of hyponatremia is potentially dangerous with risk of serious neurologic complications. Brain adaptations reducing risk of cerebral edema make the brain vulnerable to injury when chronic hyponatremia is too rapidly corrected, which is known as osmotic demyelination syndrome (ODS). To avoid complications, monitor serum sodium and chloride concentrations, fluid status, acid-base balance, and signs of neurologic complications.

Hypernatremia

Hypernatremia may occur with Sodium Chloride Injection, USP. Conditions that may increase the risk of hypernatremia, fluid overload and edema (central and peripheral), include patients with: primary hyperaldosteronism; secondary hyperaldosteronism

associated with, for example, hypertension, congestive heart failure, liver disease (including cirrhosis), renal disease (including renal artery stenosis, nephrosclerosis); and pre-eclampsia.

Certain medications, such as corticosteroids or corticotropin, may also increase risk of sodium and fluid retention, see DRUG INTERACTIONS.

Avoid Sodium Chloride Injection, USP in patients with, or at risk for, hypernatremia. If use cannot be avoided, monitor serum sodium concentrations.

Rapid correction of hypernatremia is potentially dangerous with risk of serious neurologic complications. Excessively rapid correction of hypernatremia is also associated with a risk for serious neurologic complications such as osmotic demyelination syndrome (ODS) with risk of seizures and cerebral edema.

PRECAUTIONS

Patients with Severe Renal Impairment

Administration of Sodium Chloride Injection, USP in patients with or at risk of severe renal impairment, may result in hypernatremia and/or fluid overload (see WARNINGS). Avoid Sodium Chloride Injection, USP in patients with severe renal impairment or conditions that may cause sodium and/or potassium retention, fluid overload, or edema. If use cannot be avoided, monitor patients with severe renal impairment for development of these adverse reactions.

Drug Interactions

Other Products that Affect Fluid and/or Electrolyte Balance

Administration of Sodium Chloride Injection, USP to patients treated concomitantly with drugs associated with sodium and fluid retention may increase the risk of hypernatremia and volume overload. Avoid use of Sodium Chloride Injection, USP in patients receiving such products, such as corticosteroids or corticotropin. If use cannot be avoided, monitor serum electrolytes, fluid balance and acid-base balance.

Lithium

Renal sodium and lithium clearance may be decreased during administration of 0.45% Sodium Chloride Injection, USP. Monitor serum lithium concentrations during concomitant use.

Renal sodium and lithium clearance may be increased during administration of 0.9% Sodium Chloride Injection, USP. Monitor serum lithium concentrations during concomitant use.

Other Drugs that Increase the Risk of Hyponatremia

Administration of Sodium Chloride Injection, USP in patients treated concomitantly with medications associated with hyponatremia may increase the risk of developing hyponatremia.

Avoid use of Sodium Chloride Injection, USP in patients receiving products, such as diuretics, and certain antiepileptic and psychotropic medications. Drugs that increase the vasopressin effect reduce renal electrolyte free water excretion and may also increase the risk of hyponatremia following treatment with intravenous fluids. If use cannot be avoided, monitor serum sodium concentrations.

Pregnancy

There are no adequate and well controlled studies with Sodium Chloride Injection, USP in pregnant women and animal reproduction studies have not been conducted with this drug. Therefore, it is not known whether Sodium Chloride Injection, USP can cause fetal harm when administered to a pregnant woman. Sodium Chloride Injection, USP should be given during pregnancy only if the potential benefit justifies the potential risk to the fetus.

Nursing Mothers

It is not known whether this drug is present in human milk. Because many drugs are present in human milk, caution should be exercised when Sodium Chloride Injection, USP is administered to a nursing woman.

Pediatric Use

The use of Sodium Chloride Injection, USP in pediatric patients is based on clinical practice. (See DOSAGE AND ADMINISTRATION).

Closely monitor plasma electrolyte concentrations in pediatric patients who may have impaired ability to regulate fluids and electrolytes. In very low birth weight infants, excessive or rapid administration of Sodium Chloride Injection, USP may result in increased serum osmolality and risk of intracerebral hemorrhage.

Children (including neonates and older children) are at increased risk of developing hyponatremia as well as for developing hyponatremic encephalopathy.

Geriatric Use

Geriatric patients are at increased risk of developing electrolyte imbalances. Sodium Chloride Injection, USP is known to be substantially excreted by the kidney, and the risk of toxic reactions to this drug may be greater in patients with impaired renal function. Therefore, dose selection for an elderly patient should be cautious, usually starting at the low end of the dosing range, reflecting the greater frequency of decreased hepatic, renal, or cardiac function, and of concomitant disease or other drug therapy. Consider monitoring renal function in elderly patients.

ADVERSE REACTIONS

Post-Marketing Adverse Reactions

The following adverse reactions have been identified during post approval use of Sodium Chloride Injection, USP. Because these reactions are reported voluntarily from a population of uncertain size, it is not always possible to reliably estimate their frequency or establish a causal relationship to drug exposure.

The following adverse reactions have been reported in the post-marketing experience during use of Sodium Chloride Injection, USP and include the following:

General disorders and administration site conditions: Infusion site erythema, injection site streaking, burning sensation, and infusion site urticaria

Hypersensitivity reactions: Hypotension, pyrexia, tremor, chills, urticaria, rash, and pruritus.

Metabolism and nutrition disorders: Hypernatremia*, hyponatremia, hyperchloremic metabolic acidosis.

Nervous System Disorders: Hyponatremic encephalopathy

* Adverse reaction of hyponatremia is only related to 0.9% Sodium Chloride Injection, USP

If an adverse reaction does occur, discontinue the infusion, evaluate the patient, institute appropriate therapeutic countermeasures and save the remainder of the fluid for examination if deemed necessary.

OVERDOSAGE

Excessive administration of:

- 0.45% Sodium Chloride Injection, USP can cause hyponatremia and hypernatremia. Both hypo- and hypernatremia can lead to CNS manifestations, including seizures, coma, cerebral edema and death.
- 0.9% Sodium Chloride Injection, USP can cause hypernatremia.
- Sodium Chloride Injection, USP can cause fluid overload (which can lead to pulmonary and/or peripheral edema). See WARNINGS and ADVERSE REACTIONS.

When assessing an overdose, any additives in the solution must also be considered. The effects of an overdose may require immediate medical attention and treatment.

Interventions include discontinuation of Sodium Chloride Injection, USP administration, dose reduction, and other measures as indicated for the specific clinical constellation (e.g., monitoring of fluid balance, electrolyte concentrations and acid base balance).

DOSAGE AND ADMINISTRATION

Important Preparation and Administration Instructions

- Sodium Chloride Injection, USP is intended for intravenous administration using sterile equipment.
- Prior to infusion, visually inspect the solution for particulate matter and discoloration. The solution should be clear, and there should be no precipitates. Do not administer unless solution is clear, and container is undamaged.
- To reduce the risk of air embolism, adhere to the following preparation instructions for Lactated Ringer’s Injection, USP:
  - Use a non-vented infusion set or close the vent on a vented set.
  - Use a dedicated line without any connections (do not connect flexible containers in series).
  - The use of pressure infusion is not recommended as a method to increase flow rates. However, if pressure infusion is required, ensure that any air within the bag is fully evacuated prior to initiation of infusion.
  - If using a pumping device to administer Sodium Chloride Injection, turn off the pump before the container is empty.
  - Do not mix or administer 0.45% Sodium Chloride Injection, USP through the same administration set with whole blood or cellular blood components.

Dosing Information

The choice of product, dosage, volume, rate, and duration of administration is dependent upon the age, weight and clinical condition of the patient and concomitant therapy, and administration should be determined by a physician experienced in intravenous fluid therapy.

Introduction of Additives

Additives may be incompatible.

Evaluate all additions to the plastic container for compatibility and stability of the resulting preparation. Consult with a pharmacist, if available.

If, in the informed judgment of the physician, it is deemed advisable to introduce additives, use aseptic technique. Mix thoroughly when additives have been introduced. After addition, if there is a discoloration and/or the appearance of precipitates, insoluble complexes or crystals, do not use. Do not store solutions containing additives. Discard any unused portion.

HOW SUPPLIED

The available sizes of each injection in VIAFLEX plastic containers are shown below:

Code | Size (mL) | NDC | Product Name
2B1313 | 500 | 0338-0043-03 | 0.45% Sodium Chloride Injection, USP
2B1314 | 1000 | 0338-0043-04
2B1300 | 25 Quad Pack | 0338-0049-10 | 0.9% Sodium Chloride Injection, USP
 | 50
2B1306 | Single pack | 0338-0049-41
2B1301 | Quad pack | 0338-0049-11
2B1308 | Multi pack | 0338-0049-31
 | 100
2B1307 | Single pack | 0338-0049-48
2B1302 | Quad pack | 0338-0049-18
2B1309 | Multi pack | 0338-0049-38
2B1321 | 150 | 0338-0049-01
2B1322 | 250 | 0338-0049-02
2B1323 | 500 | 0338-0049-03
2B1324 | 1000 | 0338-0049-04

Exposure of pharmaceutical products to heat should be minimized. Avoid excessive heat. It is recommended the product be stored at room temperature (25°C/77°F); brief exposure up to 40°C/104°F does not adversely affect the product.

DIRECTIONS FOR USE OF VIAFLEX PLASTIC CONTAINER

For Information on Risk of Air Embolism – see DOSAGE AND ADMINISTRATION.

To Open

Tear overwrap down side at slit and remove solution container. Visually inspect the container. If the outlet port protector is damaged, detached, or not present, discard container as solution path sterility may be impaired. Some opacity of the plastic due to moisture absorption during the sterilization process may be observed. This is normal and does not affect the solution quality or safety. The opacity will diminish gradually. Check for minute leaks by squeezing inner bag firmly. If leaks are found, discard solution as sterility may be impaired. If supplemental medication is desired, follow directions below.

Preparation for Administration

1. Suspend container from eyelet support.
2. Remove protector from outlet port at bottom of container.
3. Attach administration set. Refer to complete directions accompanying set.

To Add Medication

Additives may be incompatible

To add medication before solution administration

1. Prepare medication site.
2. Using syringe with 19 to 22 gauge needle, puncture resealable medication port and inject.
3. Mix solution and medication thoroughly. For high density medication such as potassium chloride, squeeze ports while ports are upright and mix thoroughly.

To add medication during solution administration

1. Close clamp on the set.
2. Prepare medication site.
3. Using syringe with 19 to 22 gauge needle, puncture resealable medication port and inject.
4. Remove container from IV pole and/or turn to an upright position.
5. Evacuate both ports by squeezing them while container is in the upright position.
6. Mix solution and medication thoroughly.
7. Return container to in-use position and continue administration.

Baxter Healthcare Corporation
Deerfield, IL 60015 USA
Printed in USA

Distributed in Canada by
Baxter Corporation
Mississauga, ON L5N 0C2

07-19-00-6066

Rev. July 2024

Baxter and Viaflex are trademarks of Baxter International Inc.

PACKAGE LABELING - PRINCIPAL DISPLAY PANEL

LOT
EXP

2B1302
NDC 0338-0049-18

0.9% Sodium Chloride Injection USP

100 mL

Single dose container
Each 100 mL contains
900 mg Sodium Chloride USP
pH 5.0 (4.5 to 7.0) mEq/100 mL
Sodium 15 Chloride 15 Osmolarity
308 mOsmol/L (calc) Sterile
Nonpyrogenic Read package insert
for full information Additives may
be incompatible Dosage
Intravenously as directed by a
physician Cautions Must not be used
in series connections Do not use
unless solution is clear Rx Only
VIAFLEX container
PL 146
Baxter VIAFLEX and PL 146 are trademarks of
Baxter International Inc

Baxter
Baxter Healthcare Corporation
Deerfiled IL 60015 USA
Made in USA

LOT EXP

281313

NDC0338-0043-03

0.45°/o Sodium Chloride
Injection USP

500ml

EACH 100 mL CONTAINS 450 rng SODIUM CHLORIDE USP
pH 5.0 (4. 5 TO 7.0) mEq/L SODIUM 77 CHLORIDE 77
HYPOTONIC OSMOLARITY 154 mQsmol/L (CALC) STERILE
NONPYROGENIC SINGLE DOSE CONTAINER ADDITIVES MAY BE INCOMPATIBLE CONSULT WITH PHARMACIST IF AVAILABLE
WHEN INTRODUCING ADDITIVES USE ASEPTIC TECHNIQUE MIX
THOROUGHLY DO NOT STORE DOSAGE INTRAVENOUSLY AS
DIRECTED BY A PHYSICIAN SEE DIRECTIONS CAUTIONS
SQUEEZE AND INSPECT INNER BAG WHICH MAINTAINS PRODUCT
STERILITY DISCARD IF LEAKS ARE FOUND MUST NOT BE USED
IN SERIES CONNECTIONS Do NOT USE UNLESS SOLUTION IS
CLEAR Rx ONLY STORE UNIT IN MOISTURE BARRIER
OVERWRAP AT ROOM TEMPERATURE (25°C/77°F) UNTIL READY
TO USE AVOID EXCESSIVE HEAT SEE INSERT

VIAFLEX CONTAINER Pl 146 PLASTIC

BAXTER VIAFLEX AND PL 146 ARE TRADEMARKS OF
BAXTER INTERNATIONAL INC

FOR PRODUCT INFORMATION 1-800-933-0303

Baxter Logo

BAXTER HEALTHCARE CORPORATION
DEERFIELD IL 60015 USA

MADE IN USA

07-25-34-139